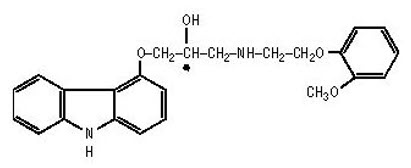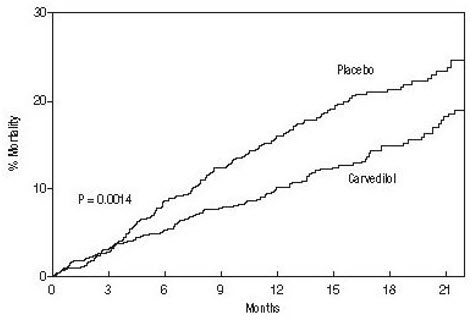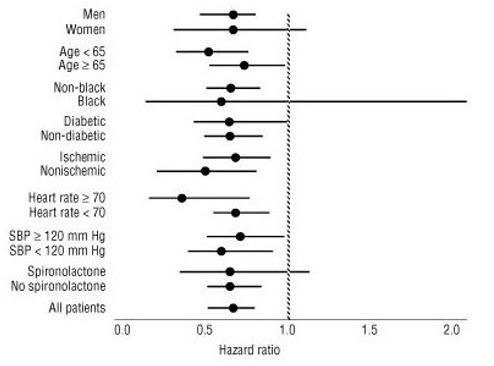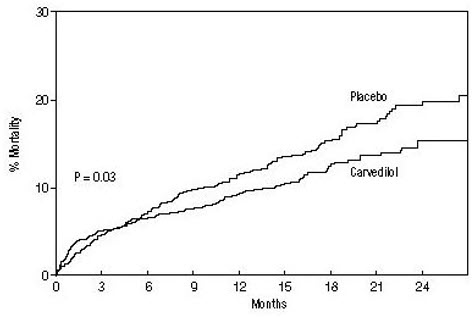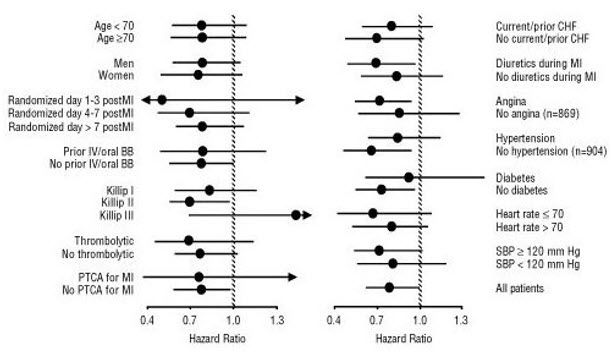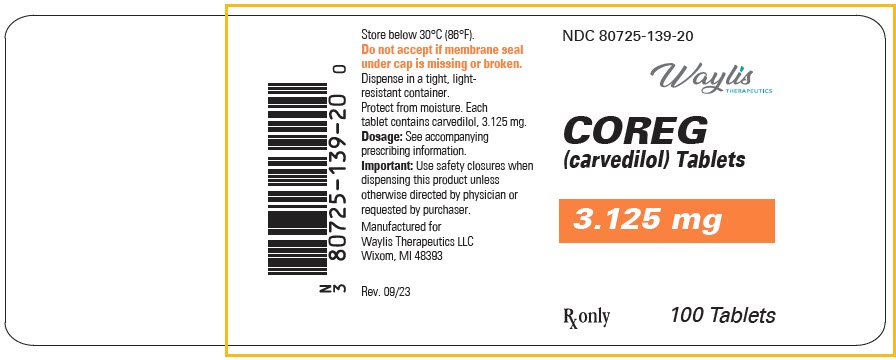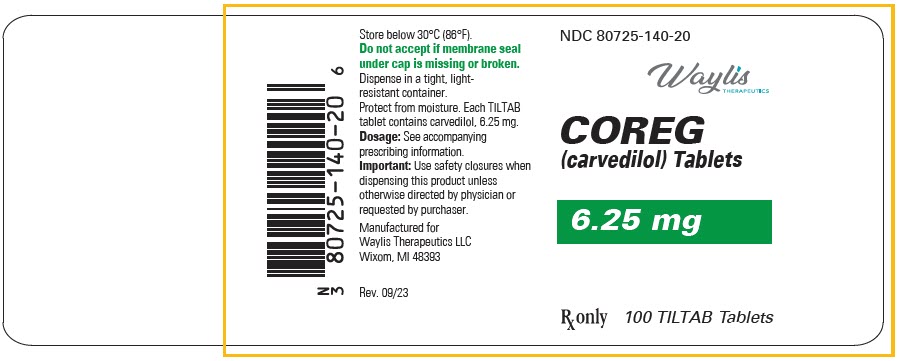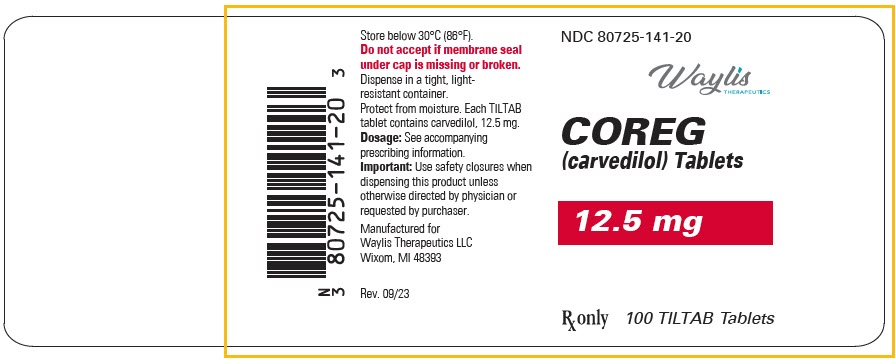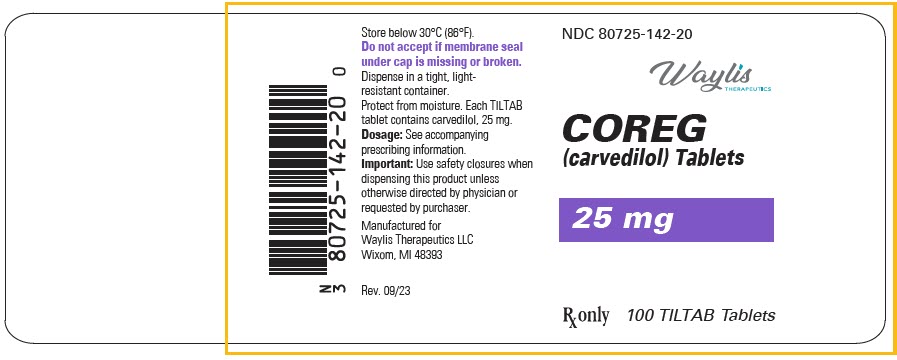 DRUG LABEL: Coreg
NDC: 80725-139 | Form: TABLET, FILM COATED
Manufacturer: Waylis Therapeutics LLC
Category: prescription | Type: HUMAN PRESCRIPTION DRUG LABEL
Date: 20250124

ACTIVE INGREDIENTS: Carvedilol 3.125 mg/1 1
INACTIVE INGREDIENTS: SILICON DIOXIDE; CROSPOVIDONE (120 .MU.M); HYPROMELLOSE, UNSPECIFIED; LACTOSE, UNSPECIFIED FORM; MAGNESIUM STEARATE; POLYETHYLENE GLYCOL, UNSPECIFIED; POLYSORBATE 80; POVIDONE, UNSPECIFIED; SUCROSE; TITANIUM DIOXIDE

HIGHLIGHTS OF PRESCRIBING INFORMATION

These highlights do not include all the information needed to use COREG safely and effectively. See full prescribing information for COREG.
COREG (carvedilol) tablets for oral use.
Initial U.S. Approval: 1995

1. INDICATIONS AND USAGE

COREG is an alpha-/beta-adrenergic blocking agent indicated for the treatment of:

- mild to severe chronic heart failure (1.1)
- left ventricular dysfunction following myocardial infarction in clinically stable patients (1.2)
- hypertension (1.3)

2 DOSAGE AND ADMINISTRATION

Take with food. Individualize dosage and monitor during up-titration. (2)

- Heart failure: Start at 3.125 mg twice daily and increase to 6.25, 12.5, and then 25mg twice daily over intervals of at least 2 weeks. Maintain lower doses if higher doses are not tolerated. (2.1)
- Left ventricular dysfunction following myocardial infarction. Start at 6.25 mg twice daily and increase to 12.5 mg then 25 mg twice daily after intervals of 3 to 10 days. A lower starting dose or slower titration may be used. (2.2)
- Hypertension: Start at 6.25 mg twice daily and increase if needed for blood pressure control to 12.5 mg and then 25 mg twice daily over intervals of 1 to 2 weeks. (2.3)

3 DOSAGE FORMS AND STRENGTHS

Tablets: 3.125 mg, 6.25 mg, 12.5 mg, 25 mg (3)

4 CONTRAINDICATIONS

- Bronchial asthma or related bronchospastic conditions. (4)
- Second- or third-degree AV block. (4)
- Sick sinus syndrome. (4)
- Severe bradycardia (unless permanent pacemaker in place). (4)
- Patients in cardiogenic shock or decompensated heart failure requiring the use of IV inotropic therapy. (4)
- Severe hepatic impairment (2.4, 4)
- History of serious hypersensitivity reaction (e.g., Stevens-Johnson syndrome, anaphylactic reaction, angioedema) to any component of this medication or other medications containing carvedilol. (4)

5 WARNINGS AND PRECAUTIONS

- Acute exacerbation of coronary artery disease upon cessation of therapy: Do not abruptly discontinue. (5.1)
- Bradycardia, hypotension, worsening heart failure/fluid retention may occur. Reduce the dose as needed. (5.2, 5.3, 5.4)
- Non-allergic bronchospasm (e.g., chronic bronchitis and emphysema). Avoid β-blockers. (4) However, if deemed necessary, use with caution and at lowest effective dose. (5.5)
- Diabetes: May mask symptoms of hypoglycemia and alter glucose levels; monitor. (5.6)

6 ADVERSE REACTIONS

Most common adverse events (6.1):

- Heart failure and left ventricular dysfunction following myocardial infarction (≤10%): Dizziness, fatigue, hypotension, diarrhea, hyperglycemia, asthenia, bradycardia, weight increase.
- Hypertension (≥5%): Dizziness.

To report SUSPECTED ADVERSE REACTIONS, contact Waylis Therapeutics LLC at 1-844-200-7910 or FDA at 1-800-FDA-1088 or www.fda.gov/medwatch.

7 DRUG INTERACTIONS

- CYP P450 2D6 enzyme inhibitors may increase and rifampin may decrease carvedilol levels. (7.1, 7.5)
- Hypotensive agents (e.g., reserpine, MAO inhibitors, clonidine) may increase the risk of hypotension and/or severe bradycardia. (7.4)
- Cyclosporine or digoxin levels may increase. (7.3, 7.4)
- Both digitalis glycosides and β-blockers slow atrioventricular conduction and decrease heart rate. Concomitant use can increase the risk of bradycardia. (7.4)
- Amiodarone may increase carvedilol levels resulting in further slowing of the heart rate or cardiac conduction. (7.6)
- Verapamil- or diltiazem-type calcium channel blockers may affect ECG and/or blood pressure. (7.7)
- Insulin and oral hypoglycemics action may be enhanced. (7.8)

FULL PRESCRIBING INFORMATION

1. INDICATIONS AND USAGE

1.1 Heart Failure

COREG is indicated for the treatment of mild-to-severe chronic heart failure of ischemic or cardiomyopathic origin, usually in addition to diuretics, ACE inhibitors, and digitalis, to increase survival and, also, to reduce the risk of hospitalization [see Drug Interactions (7.4), Clinical Studies (14.1)].

1.2 Left Ventricular Dysfunction following Myocardial Infarction

COREG is indicated to reduce cardiovascular mortality in clinically stable patients who have survived the acute phase of a myocardial infarction and have a left ventricular ejection fraction of less than or equal to 40% (with or without symptomatic heart failure) [see Clinical Studies (14.2)].

1.3 Hypertension

COREG is indicated for the management of essential hypertension [see Clinical Studies (14.3, 14.4)]. It can be used alone or in combination with other antihypertensive agents, especially thiazide-type diuretics [see Drug Interactions (7.2)].

2 DOSAGE AND ADMINISTRATION

COREG should be taken with food to slow the rate of absorption and reduce the incidence of orthostatic effects.

2.1 Heart Failure

DOSAGE MUST BE INDIVIDUALIZED AND CLOSELY MONITORED BY A PHYSICIAN DURING UP-TITRATION. Prior to initiation of COREG, it is recommended that fluid retention be minimized. The recommended starting dose of COREG is 3.125 mg twice daily for 2 weeks. If tolerated, patients may have their dose increased to 6.25, 12.5, and 25 mg twice daily over successive intervals of at least 2 weeks. Patients should be maintained on lower doses if higher doses are not tolerated. A maximum dose of 50 mg twice daily has been administered to patients with mild-to-moderate heart failure weighing over 85 kg (187 lbs.).

Patients should be advised that initiation of treatment and (to a lesser extent) dosage increases may be associated with transient symptoms of dizziness or lightheadedness (and rarely syncope) within the first hour after dosing. During these periods, patients should avoid situations such as driving or hazardous tasks, where symptoms could result in injury. Vasodilatory symptoms often do not require treatment, but it may be useful to separate the time of dosing of COREG from that of the ACE inhibitor or to reduce temporarily the dose of the ACE inhibitor. The dose of COREG should not be increased until symptoms of worsening heart failure or vasodilation have been stabilized.

Fluid retention (with or without transient worsening heart failure symptoms) should be treated by an increase in the dose of diuretics.

The dose of COREG should be reduced if patients experience bradycardia (heart rate less than 55 beats per minute).

Episodes of dizziness or fluid retention during initiation of COREG can generally be managed without discontinuation of treatment and do not preclude subsequent successful titration of, or a favorable response to, carvedilol.

2.2 Left Ventricular Dysfunction following Myocardial Infarction

DOSAGE MUST BE INDIVIDUALIZED AND MONITORED DURING UP-TITRATION.

Treatment with COREG may be started as an inpatient or outpatient and should be started after the patient is hemodynamically stable and fluid retention has been minimized. It is recommended that COREG be started at 6.25 mg twice daily and increased after 3 to 10 days, based on tolerability, to 12.5 mg twice daily, then again to the target dose of 25 mg twice daily. A lower starting dose may be used (3.125 mg twice daily) and/or the rate of up-titration may be slowed if clinically indicated (e.g., due to low blood pressure or heart rate, or fluid retention). Patients should be maintained on lower doses if higher doses are not tolerated. The recommended dosing regimen need not be altered in patients who received treatment with an IV or oral β-blocker during the acute phase of the myocardial infarction.

2.3 Hypertension

DOSAGE MUST BE INDIVIDUALIZED. The recommended starting dose of COREG is 6.25 mg twice daily. If this dose is tolerated, using standing systolic pressure measured about 1 hour after dosing as a guide, the dose should be maintained for 7 to 14 days, and then increased to 12.5 mg twice daily if needed, based on trough blood pressure, again using standing systolic pressure 1 hour after dosing as a guide for tolerance. This dose should also be maintained for 7 to 14 days and can then be adjusted upward to 25 mg twice daily if tolerated and needed. The full antihypertensive effect of COREG is seen within 7 to 14 days. Total daily dose should not exceed 50 mg.

Concomitant administration with a diuretic can be expected to produce additive effects and exaggerate the orthostatic component of carvedilol action.

2.4 Hepatic Impairment

COREG should not be given to patients with severe hepatic impairment [see Contraindications (4)].

3 DOSAGE FORMS AND STRENGTHS

The white, oval, film‑coated tablets are available in the following strengths:

- 3.125 mg – engraved with "39" and "WP"
- 6.25 mg – engraved with "4140" and "WP"
- 12.5 mg – engraved with "4141" and "WP"
- 25 mg – engraved with "4142" and "WP"

4 CONTRAINDICATIONS

COREG is contraindicated in the following conditions:

- Bronchial asthma or related bronchospastic conditions. Deaths from status asthmaticus have been reported following single doses of COREG.
- Second- or third-degree AV block.
- Sick sinus syndrome.
- Severe bradycardia (unless a permanent pacemaker is in place).
- Patients with cardiogenic shock or who have decompensated heart failure requiring the use of intravenous inotropic therapy. Such patients should first be weaned from intravenous therapy before initiating COREG.
- Patients with severe hepatic impairment.
- Patients with a history of a serious hypersensitivity reaction (e.g., Stevens-Johnson syndrome, anaphylactic reaction, angioedema) to any component of this medication or other medications containing carvedilol.

5 WARNINGS AND PRECAUTIONS

5.1 Cessation of Therapy

Patients with coronary artery disease, who are being treated with COREG, should be advised against abrupt discontinuation of therapy. Severe exacerbation of angina and the occurrence of myocardial infarction and ventricular arrhythmias have been reported in patients with angina following the abrupt discontinuation of therapy with β-blockers.

The last 2 complications may occur with or without preceding exacerbation of the angina pectoris. As with other β-blockers, when discontinuation of COREG is planned, the patients should be carefully observed and advised to limit physical activity to a minimum. COREG should be discontinued over 1 to 2 weeks whenever possible. If the angina worsens or acute coronary insufficiency develops, it is recommended that COREG be promptly reinstituted, at least temporarily. Because coronary artery disease is common and may be unrecognized, it may be prudent not to discontinue therapy with COREG abruptly even in patients treated only for hypertension or heart failure.

5.2 Bradycardia

In clinical trials, COREG caused bradycardia in about 2% of hypertensive subjects, 9% of subjects with heart failure, and 6.5% of subjects with myocardial infarction and left ventricular dysfunction. If pulse rate drops below 55 beats per minute, the dosage should be reduced.

5.3 Hypotension

In clinical trials of primarily mild‑to‑moderate heart failure, hypotension and postural hypotension occurred in 9.7% and syncope in 3.4% of subjects receiving COREG compared with 3.6% and 2.5% of placebo subjects, respectively. The risk for these events was highest during the first 30 days of dosing, corresponding to the up‑titration period and was a cause for discontinuation of therapy in 0.7% of subjects receiving COREG, compared with 0.4% of placebo subjects. In a long‑term, placebo‑controlled trial in severe heart failure (COPERNICUS), hypotension and postural hypotension occurred in 15.1% and syncope in 2.9% of heart failure subjects receiving COREG compared with 8.7% and 2.3% of placebo subjects, respectively. These events were a cause for discontinuation of therapy in 1.1% of subjects receiving COREG, compared with 0.8% of placebo subjects.

Postural hypotension occurred in 1.8% and syncope in 0.1% of hypertensive subjects, primarily following the initial dose or at the time of dose increase and was a cause for discontinuation of therapy in 1% of subjects.

In the CAPRICORN trial of survivors of an acute myocardial infarction, hypotension or postural hypotension occurred in 20.2% of subjects receiving COREG compared with 12.6% of placebo subjects. Syncope was reported in 3.9% and 1.9% of subjects, respectively. These events were a cause for discontinuation of therapy in 2.5% of subjects receiving COREG, compared with 0.2% of placebo subjects.

Starting with a low dose, administration with food, and gradual up-titration should decrease the likelihood of syncope or excessive hypotension [see Dosage and Administration (2.1, 2.2, 2.3)]. During initiation of therapy, the patient should be cautioned to avoid situations such as driving or hazardous tasks, where injury could result should syncope occur.

5.4 Heart Failure/Fluid Retention

Worsening heart failure or fluid retention may occur during up-titration of carvedilol. If such symptoms occur, diuretics should be increased and the carvedilol dose should not be advanced until clinical stability resumes [see Dosage and Administration (2)].

Occasionally it is necessary to lower the carvedilol dose or temporarily discontinue it.

Such episodes do not preclude subsequent successful titration of, or a favorable response to, carvedilol. In a placebo-controlled trial of subjects with severe heart failure, worsening heart failure during the first 3 months was reported to a similar degree with carvedilol and with placebo. When treatment was maintained beyond 3 months, worsening heart failure was reported less frequently in subjects treated with carvedilol than with placebo. Worsening heart failure observed during long-term therapy is more likely to be related to the patients' underlying disease than to treatment with carvedilol.

5.5 Non-allergic Bronchospasm

Patients with bronchospastic disease (e.g., chronic bronchitis, emphysema) should, in general, not receive β-blockers. COREG may be used with caution, however, in patients who do not respond to, or cannot tolerate, other antihypertensive agents. It is prudent, if COREG is used, to use the smallest effective dose, so that inhibition of endogenous or exogenous β-agonists is minimized.

In clinical trials of subjects with heart failure, subjects with bronchospastic disease were enrolled if they did not require oral or inhaled medication to treat their bronchospastic disease. In such patients, it is recommended that carvedilol be used with caution. The dosing recommendations should be followed closely and the dose should be lowered if any evidence of bronchospasm is observed during up-titration.

5.6 Effects on Blood Sugar

Beta-blockers may prevent early warning signs of hypoglycemia, such as tachycardia, and increase the risk for severe or prolonged hypoglycemia at any time during treatment, especially in patients with diabetes mellitus or children and patients who are fasting (i.e., surgery, not eating regularly, or are vomiting). If severe hypoglycemia occurs, patients should be instructed to seek emergency treatment.

In patients with heart failure and diabetes, carvedilol therapy may lead to worsening hyperglycemia, which responds to intensification of hypoglycemic therapy. It is recommended that blood glucose be monitored when carvedilol dosing is initiated, adjusted, or discontinued. Trials designed to examine the effects of carvedilol on glycemic control in patients with diabetes and heart failure have not been conducted.

In a trial designed to examine the effects of carvedilol on glycemic control in a population with mild-to-moderate hypertension and well-controlled type 2 diabetes mellitus, carvedilol had no adverse effect on glycemic control, based on HbA1c measurements [see Clinical Studies (14.4)].

5.7 Peripheral Vascular Disease

β-blockers can precipitate or aggravate symptoms of arterial insufficiency in patients with peripheral vascular disease. Caution should be exercised in such individuals.

5.8 Deterioration of Renal Function

Rarely, use of carvedilol in patients with heart failure has resulted in deterioration of renal function. Patients at risk appear to be those with low blood pressure (systolic blood pressure less than 100 mm Hg), ischemic heart disease and diffuse vascular disease, and/or underlying renal insufficiency. Renal function has returned to baseline when carvedilol was stopped. In patients with these risk factors, it is recommended that renal function be monitored during up-titration of carvedilol and the drug discontinued or dosage reduced if worsening of renal function occurs.

5.9 Major Surgery

Chronically administered β-blocking therapy should not be routinely withdrawn prior to major surgery; however, the impaired ability of the heart to respond to reflex adrenergic stimuli may augment the risks of general anesthesia and surgical procedures.

5.10 Thyrotoxicosis

β-adrenergic blockade may mask clinical signs of hyperthyroidism, such as tachycardia. Abrupt withdrawal of β-blockade may be followed by an exacerbation of the symptoms of hyperthyroidism or may precipitate thyroid storm.

5.11 Pheochromocytoma

In patients with pheochromocytoma, an α-blocking agent should be initiated prior to the use of any β-blocking agent. Although carvedilol has both α- and β-blocking pharmacologic activities, there has been no experience with its use in this condition.

Therefore, caution should be taken in the administration of carvedilol to patients suspected of having pheochromocytoma.

5.12 Prinzmetal's Variant Angina

Agents with non-selective β-blocking activity may provoke chest pain in patients with Prinzmetal's variant angina. There has been no clinical experience with carvedilol in these patients although the α-blocking activity may prevent such symptoms. However, caution should be taken in the administration of carvedilol to patients suspected of having Prinzmetal's variant angina.

5.13 Risk of Anaphylactic Reaction

While taking β-blockers, patients with a history of severe anaphylactic reaction to a variety of allergens may be more reactive to repeated challenge, either accidental, diagnostic, or therapeutic. Such patients may be unresponsive to the usual doses of epinephrine used to treat allergic reaction.

5.14 Intraoperative Floppy Iris Syndrome

Intraoperative Floppy Iris Syndrome (IFIS) has been observed during cataract surgery in some patients treated with alpha-1 blockers (COREG is an alpha/beta blocker). This variant of small pupil syndrome is characterized by the combination of a flaccid iris that billows in response to intraoperative irrigation currents, progressive intraoperative miosis despite preoperative dilation with standard mydriatic drugs, and potential prolapse of the iris toward the phacoemulsification incisions. The patient's ophthalmologist should be prepared for possible modifications to the surgical technique, such as utilization of iris hooks, iris dilator rings, or viscoelastic substances. There does not appear to be a benefit of stopping alpha-1 blocker therapy prior to cataract surgery.

6 ADVERSE REACTIONS

6.1 Clinical Studies Experience

Because clinical trials are conducted under widely varying conditions, adverse reaction rates observed in the clinical trials of a drug cannot be directly compared with rates in the clinical trials of another drug and may not reflect the rates observed in practice.

COREG has been evaluated for safety in subjects with heart failure (mild, moderate, and severe), in subjects with left ventricular dysfunction following myocardial infarction and in hypertensive subjects The observed adverse event profile was consistent with the pharmacology of the drug and the health status of the subjects in the clinical trials. Adverse events reported for each of these patient populations are provided below. Excluded are adverse events considered too general to be informative, and those not reasonably associated with the use of the drug because they were associated with the condition being treated or are very common in the treated population. Rates of adverse events were generally similar across demographic subsets (men and women, elderly and non-elderly, blacks and non-blacks).

Heart Failure

COREG has been evaluated for safety in heart failure in more than 4,500 subjects worldwide of whom more than 2,100 participated in placebo-controlled clinical trials. Approximately 60% of the total treated population in placebo-controlled clinical trials received COREG for at least 6 months and 30% received COREG for at least 12 months. In the COMET trial, 1,511 subjects with mild-to-moderate heart failure were treated with COREG for up to 5.9 years (mean: 4.8 years). Both in U.S. clinical trials in mild-to- moderate heart failure that compared COREG in daily doses up to 100 mg (n = 765) with placebo (n = 437), and in a multinational clinical trial in severe heart failure (COPERNICUS) that compared COREG in daily doses up to 50 mg (n = 1,156) with placebo (n = 1,133), discontinuation rates for adverse experiences were similar in carvedilol and placebo subjects. In placebo-controlled clinical trials, the only cause of discontinuation greater than 1% and occurring more often on carvedilol was dizziness (1.3% on carvedilol, 0.6% on placebo in the COPERNICUS trial).

Table 1 shows adverse events reported in subjects with mild‑to‑moderate heart failure enrolled in U.S. placebo‑controlled clinical trials, and with severe heart failure enrolled in the COPERNICUS trial. Shown are adverse events that occurred more frequently in drug‑treated subjects than placebo‑treated subjects with an incidence of greater than 3% in subjects treated with carvedilol regardless of causality. Median trial medication exposure was 6.3 months for both carvedilol and placebo subjects in the trials of mild‑to‑moderate heart failure and 10.4 months in the trial of subjects with severe heart failure. The adverse event profile of COREG observed in the long-term COMET trial was generally similar to that observed in the U.S. Heart Failure Trials.

Table 1. Adverse Events (%) Occurring More Frequently with COREG than with Placebo in Subjects with Mild-to-Moderate Heart Failure (HF) Enrolled in U.S. Heart Failure Trials or in Subjects with Severe Heart Failure in the COPERNICUS Trial (Incidence >3% in Subjects Treated with Carvedilol, Regardless of Causality)
Body System/ Adverse Event | Mild-to-Moderate HF |  | Severe HF
Body System/ Adverse Event | COREG | Placebo | COREG | Placebo
Body System/ Adverse Event | (n = 765) | (n = 437) | (n = 1,156) | (n = 1,133)
Body as a Whole
Asthenia | 7 | 7 | 11 | 9
Fatigue | 24 | 22 | — | —
Digoxin level increased | 5 | 4 | 2 | 1
Edema generalized | 5 | 3 | 6 | 5
Edema dependent | 4 | 2 | — | —
Cardiovascular
Bradycardia | 9 | 1 | 10 | 3
Hypotension | 9 | 3 | 14 | 8
Syncope | 3 | 3 | 8 | 5
Angina pectoris | 2 | 3 | 6 | 4
Central Nervous System
Dizziness | 32 | 19 | 24 | 17
Headache | 8 | 7 | 5 | 3
Gastrointestinal
Diarrhea | 12 | 6 | 5 | 3
Nausea | 9 | 5 | 4 | 3
Vomiting | 6 | 4 | 1 | 2
Metabolic
Hyperglycemia | 12 | 8 | 5 | 3
Weight increase | 10 | 7 | 12 | 11
BUN increased | 6 | 5 | — | —
NPN increased | 6 | 5 | — | —
Hypercholesterolemia | 4 | 3 | 1 | 1
Edema peripheral | 2 | 1 | 7 | 6
Musculoskeletal
Arthralgia | 6 | 5 | 1 | 1
Respiratory
Cough increased | 8 | 9 | 5 | 4
Rales | 4 | 4 | 4 | 2
Vision
Vision abnormal | 5 | 2 | — | —

Cardiac failure and dyspnea were also reported in these trials, but the rates were equal or greater in subjects who received placebo.

The following adverse events were reported with a frequency of greater than 1% but less than or equal to 3% and more frequently with COREG in either the U.S. placebo‑controlled trials in subjects with mild‑to‑moderate heart failure or in subjects with severe heart failure in the COPERNICUS trial.

Incidence greater than 1% to less than or equal to 3%

Body as a Whole: Allergy, malaise, hypovolemia, fever, leg edema.

Cardiovascular: Fluid overload, postural hypotension, aggravated angina pectoris, AV block, palpitation, hypertension.

Central and Peripheral Nervous System: Hypesthesia, vertigo, paresthesia.

Gastrointestinal: Melena, periodontitis.

Liver and Biliary System: SGPT increased, SGOT increased.

Metabolic and Nutritional: Hyperuricemia, hypoglycemia, hyponatremia, increased alkaline phosphatase, glycosuria, hypervolemia, diabetes mellitus, GGT increased, weight loss, hyperkalemia, creatinine increased.

Musculoskeletal: Muscle cramps.

Platelet, Bleeding, and Clotting: Prothrombin decreased, purpura, thrombocytopenia.

Psychiatric: Somnolence.

Reproductive, male: Impotence.

Special Senses: Blurred vision.

Urinary System: Renal insufficiency, albuminuria, hematuria.

Left Ventricular Dysfunction following Myocardial Infarction

COREG has been evaluated for safety in survivors of an acute myocardial infarction with left ventricular dysfunction in the CAPRICORN trial which involved 969 subjects who received COREG and 980 who received placebo. Approximately 75% of the subjects received COREG for at least 6 months and 53% received COREG for at least 12 months. Subjects were treated for an average of 12.9 months and 12.8 months with COREG and placebo, respectively.

The most common adverse events reported with COREG in the CAPRICORN trial were consistent with the profile of the drug in the U.S. heart failure trials and the COPERNICUS trial. The only additional adverse events reported in CAPRICORN in greater than 3% of the subjects and more commonly on carvedilol were dyspnea, anemia, and lung edema. The following adverse events were reported with a frequency of greater than 1% but less than or equal to 3% and more frequently with COREG: flu syndrome, cerebrovascular accident, peripheral vascular disorder, hypotonia, depression, gastrointestinal pain, arthritis, and gout. The overall rates of discontinuations due to adverse events were similar in both groups of subjects. In this database, the only cause of discontinuation greater than 1% and occurring more often on carvedilol was hypotension (1.5% on carvedilol, 0.2% on placebo).

Hypertension

COREG has been evaluated for safety in hypertension in more than 2,193 subjects in U.S. clinical trials and in 2,976 subjects in international clinical trials. Approximately 36% of the total treated population received COREG for at least 6 months. Most adverse events reported during therapy with COREG were of mild to moderate severity. In U.S. controlled clinical trials directly comparing COREG in doses up to 50 mg (n = 1,142) with placebo (n = 462), 4.9% of subjects receiving COREG discontinued for adverse events versus 5.2% of placebo subjects. Although there was no overall difference in discontinuation rates, discontinuations were more common in the carvedilol group for postural hypotension (1% versus 0). The overall incidence of adverse events in U.S. placebo‑controlled trials increased with increasing dose of COREG. For individual adverse events this could only be distinguished for dizziness, which increased in frequency from 2% to 5% as total daily dose increased from 6.25 mg to 50 mg.

Table 2 shows adverse events in U.S. placebo‑controlled clinical trials for hypertension that occurred with an incidence of greater than or equal to 1% regardless of causality and that were more frequent in drug‑treated subjects than placebo‑treated subjects.

Table 2. Adverse Events (%) Occurring in U.S. Placebo-Controlled Hypertension Trials (Incidence ≥1%, Regardless of Causality) [Shown are events with rate >1% rounded to nearest integer.]
Body System/Adverse Event | COREG | Placebo
Body System/Adverse Event | (n = 1,142) | (n = 462)
Cardiovascular
Bradycardia | 2 | —
Postural hypotension | 2 | —
Peripheral edema | 1 | —
Central Nervous System
Dizziness | 6 | 5
Insomnia | 2 | 1
Gastrointestinal
Diarrhea | 2 | 1
Hematologic
Thrombocytopenia | 1 | —
Metabolic
Hypertriglyceridemia | 1 | —

Dyspnea and fatigue were also reported in these trials, but the rates were equal or greater in subjects who received placebo.

The following adverse events not described above were reported as possibly or probably related to COREG in worldwide open or controlled trials with COREG in subjects with hypertension or heart failure.

Incidence greater than 0.1% to less than or equal to 1%

Cardiovascular: Peripheral ischemia, tachycardia.

Central and Peripheral Nervous System: Hypokinesia.

Gastrointestinal: Bilirubinemia, increased hepatic enzymes (0.2% of hypertension patients and 0.4% of heart failure patients were discontinued from therapy because of increases in hepatic enzymes) [see Adverse Reactions (6.2)].

Psychiatric: Nervousness, sleep disorder, aggravated depression, impaired concentration, abnormal thinking, paroniria, emotional lability.

Respiratory System: Asthma [see Contraindications (4)].

Reproductive, male: Decreased libido.

Skin and Appendages: Pruritus, rash erythematous, rash maculopapular, rash psoriaform, photosensitivity reaction.

Special Senses: Tinnitus.

Urinary System: Micturition frequency increased.

Autonomic Nervous System: Dry mouth, sweating increased.

Metabolic and Nutritional: Hypokalemia, hypertriglyceridemia.

Hematologic: Anemia, leukopenia.

The following events were reported in less than or equal to 0.1% of subjects and are potentially important: complete AV block, bundle branch block, myocardial ischemia, cerebrovascular disorder, convulsions, migraine, neuralgia, paresis, anaphylactoid reaction, alopecia, exfoliative dermatitis, amnesia, GI hemorrhage, bronchospasm, pulmonary edema, decreased hearing, respiratory alkalosis, increased BUN, decreased HDL, pancytopenia, and atypical lymphocytes.

Laboratory Abnormalities

Reversible elevations in serum transaminases (ALT or AST) have been observed during treatment with COREG. Rates of transaminase elevations (2 to 3 times the upper limit of normal) observed during controlled clinical trials have generally been similar between subjects treated with COREG and those treated with placebo. However, transaminase elevations, confirmed by rechallenge, have been observed with COREG. In a long-term, placebo- controlled trial in severe heart failure, subjects treated with COREG had lower values for hepatic transaminases than subjects treated with placebo, possibly because improvements in cardiac function induced by COREG led to less hepatic congestion and/or improved hepatic blood flow.

COREG has not been associated with clinically significant changes in serum potassium, total triglycerides, total cholesterol, HDL cholesterol, uric acid, blood urea nitrogen, or creatinine. No clinically relevant changes were noted in fasting serum glucose in hypertensive patients; fasting serum glucose was not evaluated in the heart failure clinical trials.

6.2 Postmarketing Experience

The following adverse reactions have been identified during post-approval use of COREG. Because these reactions are reported voluntarily from a population of uncertain size, it is not always possible to reliably estimate their frequency or establish a causal relationship to drug exposure.

Blood and Lymphatic System Disorders

Aplastic anemia.

Immune System Disorders

Hypersensitivity (e.g., anaphylactic reactions, angioedema, urticaria).

Renal and Urinary Disorders

Urinary incontinence.

Respiratory, Thoracic, and Mediastinal Disorders

Interstitial pneumonitis.

Skin and Subcutaneous Tissue Disorders

Stevens-Johnson syndrome, toxic epidermal necrolysis, erythema multiforme.

7 DRUG INTERACTIONS

7.1 CYP2D6 Inhibitors and Poor Metabolizers

Interactions of carvedilol with potent inhibitors of CYP2D6 isoenzyme (such as quinidine, fluoxetine, paroxetine, and propafenone) have not been studied, but these drugs would be expected to increase blood levels of the R(+) enantiomer of carvedilol [see Clinical Pharmacology (12.3)]. Retrospective analysis of side effects in clinical trials showed that poor 2D6 metabolizers had a higher rate of dizziness during up-titration, presumably resulting from vasodilating effects of the higher concentrations of the α-blocking R(+) enantiomer.

7.2 Hypotensive Agents

Patients taking a β-blocker and a drug that can deplete catecholamines (e.g., reserpine and monoamine oxidase inhibitors) should be observed closely for signs of hypotension and/or severe bradycardia.

Concomitant administration of clonidine with a β-blocker may cause hypotension and bradycardia. When concomitant treatment with a β-blocker and clonidine is to be terminated, the β-blocker should be discontinued first. Clonidine therapy can then be discontinued several days later by gradually decreasing the dosage.

7.3 Cyclosporine

Modest increases in mean trough cyclosporine concentrations were observed following initiation of carvedilol treatment in 21 renal transplant subjects suffering from chronic vascular rejection. In about 30% of subjects, the dose of cyclosporine had to be reduced in order to maintain cyclosporine concentrations within the therapeutic range, while in the remainder no adjustment was needed. On the average for the group, the dose of cyclosporine was reduced about 20% in these subjects. Due to wide interindividual variability in the dose adjustment required, it is recommended that cyclosporine concentrations be monitored closely after initiation of carvedilol therapy and that the dose of cyclosporine be adjusted as appropriate.

7.4 Digitalis Glycosides

Both digitalis glycosides and β-blockers slow atrioventricular conduction and decrease heart rate. Concomitant use can increase the risk of bradycardia. Digoxin concentrations are increased by about 15% when digoxin and carvedilol are administered concomitantly. Therefore, increased monitoring of digoxin is recommended when initiating, adjusting, or discontinuing COREG [see Clinical Pharmacology (12.5)].

7.5 Inducers/Inhibitors of Hepatic Metabolism

Rifampin reduced plasma concentrations of carvedilol by about 70% [see Clinical Pharmacology (12.5)]. Cimetidine increased AUC by about 30% but caused no change in Cmax [see Clinical Pharmacology (12.5)].

7.6 Amiodarone

Amiodarone and its metabolite desethyl amiodarone, inhibitors of CYP2C9, and P- glycoprotein increased concentrations of the S(-)-enantiomer of carvedilol by at least 2 fold [see Clinical Pharmacology (12.5)]. The concomitant administration of amiodarone or other CYP2C9 inhibitors such as fluconazole with COREG may enhance the β-blocking activity resulting in further slowing of the heart rate or cardiac conduction. Patients should be observed for signs of bradycardia or heart block, particularly when one agent is added to pre-existing treatment with the other.

7.7 Calcium Channel Blockers

Conduction disturbance (rarely with hemodynamic compromise) has been observed when COREG is coadministered with diltiazem. As with other β-blockers, if COREG is administered with calcium channel blockers of the verapamil or diltiazem type, it is recommended that ECG and blood pressure be monitored.

7.8 Insulin or Oral Hypoglycemics

β-blockers may enhance the blood-sugar-reducing effect of insulin and oral hypoglycemics. Therefore, in patients taking insulin or oral hypoglycemics, regular monitoring of blood glucose is recommended [see Warnings and Precautions (5.6)].

7.9 Anesthesia

If treatment with COREG is to be continued perioperatively, particular care should be taken when anesthetic agents that depress myocardial function, such as ether, cyclopropane, and trichloroethylene, are used [see Overdosage (10)].

8 USE IN SPECIFIC POPULATIONS

8.1 Pregnancy

Risk Summary

Available data regarding use of COREG in pregnant women are insufficient to determine whether there are drug-associated risks of adverse developmental outcomes. There are risks to the mother and fetus associated with poorly controlled hypertension in pregnancy. The use of beta blockers during the third trimester of pregnancy may increase the risk of hypotension, bradycardia, hypoglycemia, and respiratory depression in the neonate [see Clinical Considerations]. In animal reproduction studies, there was no evidence of adverse developmental outcomes at clinically relevant doses [see Data]. Oral administration of carvedilol to pregnant rats during organogenesis resulted in post- implantation loss, decreased fetal body weight, and an increased frequency of delayed fetal skeletal development at maternally toxic doses that were 50 times the maximum recommended human dose (MRHD). In addition, oral administration of carvedilol to pregnant rabbits during organogenesis resulted in increased post-implantation loss at doses 25 times the MRHD [see Data].

The estimated background risk of major birth defects and miscarriage for the indicated populations are unknown. All pregnancies have a background risk of birth defect, loss, or other adverse outcomes. In the U.S. general population, the estimated background risk of major birth defects and miscarriage in clinically recognized pregnancies is 2% to 4% and 15% to 20%, respectively.

Clinical Considerations

Disease-Associated Maternal and/or Embryo-Fetal Risk: Hypertension in pregnancy increases the maternal risk for pre-eclampsia, gestational diabetes, premature delivery, and delivery complications (e.g., need for cesarean section and post-partum hemorrhage). Hypertension increases the fetal risk for intrauterine growth restriction and intrauterine death. Pregnant women with hypertension should be carefully monitored and managed accordingly.

Fetal/Neonatal Adverse Reactions: Neonates of women with hypertension who are treated with beta-blockers during the third trimester of pregnancy may be at increased risk for hypotension, bradycardia, hypoglycemia, and respiratory depression. Observe newborns for symptoms of hypotension, bradycardia, hypoglycemia, and respiratory depression and manage accordingly.

Data

Animal Data: Studies performed in rats and rabbits given carvedilol during fetal organogenesis revealed increased post‑implantation loss in rats at a maternally toxic dose of 300 mg per kg per day (50 times the MRHD as mg per m2) and in rabbits (in the absence of maternal toxicity) at doses of 75 mg per kg per day (25 times the MRHD as mg per m2). In the rats, there was also a decrease in fetal body weight at 300 mg per kg per day (50 times the MRHD as mg per m2) accompanied by an increased incidence of fetuses with delayed skeletal development. In rats, the no-effect level for embryo-fetal toxicity was 60 mg per kg per day (10 times the MRHD as mg per m2); in rabbits, it was 15 mg per kg per day (5 times the MRHD as mg per m2). In a pre- and post-natal development study in rats administered carvedilol from late gestation through lactation, increased embryo-lethality was observed at a maternally toxic dose of 200 mg per kg per day (approximately 32 times the MRHD as mg per m2), and pup mortality and delays in physical growth/development were observed at 60 mg per kg per day (10 times the MRHD as mg per m2) in the absence of maternal toxicity. The no-effect level was 12 mg per kg per day (2 times the MRHD as mg per m2). Carvedilol was present in fetal rat tissue.

8.2 Lactation

Risk Summary

There are no data on the presence of carvedilol in human milk, the effects on the breastfed infant, or the effects on milk production. Carvedilol is present in the milk of lactating rats. The developmental and health benefits of breastfeeding should be considered along with the mother's clinical need for COREG and any potential adverse effects on the breastfed infant from COREG or from the underlying maternal condition.

8.4 Pediatric Use

Effectiveness of COREG in patients younger than 18 years has not been established.

In a double-blind trial, 161 children (mean age: 6 years; range: 2 months to 17 years; 45% younger than 2 years) with chronic heart failure [NYHA class II-IV, left ventricular ejection fraction less than 40% for children with a systemic left ventricle (LV), and moderate-severe ventricular dysfunction qualitatively by echo for those with a systemic ventricle that was not an LV] who were receiving standard background treatment were randomized to placebo or to 2 dose levels of carvedilol. These dose levels produced placebo-corrected heart rate reduction of 4 to 6 heart beats per minute, indicative of β- blockade activity. Exposure appeared to be lower in pediatric subjects than adults. After 8 months of follow-up, there was no significant effect of treatment on clinical outcomes. Adverse reactions in this trial that occurred in greater than 10% of subjects treated with COREG and at twice the rate of placebo-treated subjects included chest pain (17% versus 6%), dizziness (13% versus 2%), and dyspnea (11% versus 0%).

8.5 Geriatric Use

Of the 765 subjects with heart failure randomized to COREG in U.S. clinical trials, 31% (235) were aged 65 years or older, and 7.3% (56) were aged 75 years or older. Of the 1,156 subjects randomized to COREG in a long‑term, placebo‑controlled trial in severe heart failure, 47% (547) were aged 65 years or older, and 15% (174) were aged 75 years or older. Of 3,025 subjects receiving COREG in heart failure trials worldwide, 42% were aged 65 years or older.

Of the 975 subjects with myocardial infarction randomized to COREG in the CAPRICORN trial, 48% (468) were aged 65 years or older, and 11% (111) were aged 75 years or older.

Of the 2,065 hypertensive subjects in U.S. clinical trials of efficacy or safety who were treated with COREG, 21% (436) were aged 65 years or older. Of 3,722 subjects receiving COREG in hypertension clinical trials conducted worldwide, 24% were aged 65 years or older.

With the exception of dizziness in hypertensive subjects (incidence 8.8% in the elderly versus 6% in younger subjects), no overall differences in the safety or effectiveness (see Figures 2 and 4) were observed between the older subjects and younger subjects in each of these populations. Similarly, other reported clinical experience has not identified differences in responses between the elderly and younger subjects, but greater sensitivity of some older individuals cannot be ruled out.

10 OVERDOSAGE

Overdosage may cause severe hypotension, bradycardia, cardiac insufficiency, cardiogenic shock, and cardiac arrest. Respiratory problems, bronchospasms, vomiting, lapses of consciousness, and generalized seizures may also occur.

The patient should be placed in a supine position and, where necessary, kept under observation and treated under intensive-care conditions. The following agents may be administered:

For excessive bradycardia: Atropine, 2 mg IV.

To support cardiovascular function: Glucagon, 5 to 10 mg IV rapidly over 30 seconds, followed by a continuous infusion of 5 mg per hour; sympathomimetics (dobutamine, isoprenaline, adrenaline) at doses according to body weight and effect.

If peripheral vasodilation dominates, it may be necessary to administer adrenaline or noradrenaline with continuous monitoring of circulatory conditions. For therapy- resistant bradycardia, pacemaker therapy should be performed. For bronchospasm, β- sympathomimetics (as aerosol or IV) or aminophylline IV should be given. In the event of seizures, slow IV injection of diazepam or clonazepam is recommended.

NOTE: In the event of severe intoxication where there are symptoms of shock, treatment with antidotes must be continued for a sufficiently long period of time consistent with the 7- to 10-hour half-life of carvedilol.

Cases of overdosage with COREG alone or in combination with other drugs have been reported. Quantities ingested in some cases exceeded 1,000 milligrams. Symptoms experienced included low blood pressure and heart rate. Standard supportive treatment was provided and individuals recovered.

11 DESCRIPTION

Carvedilol is a nonselective β-adrenergic blocking agent with α1-blocking activity. It is (±)-1-(Carbazol-4-yloxy)-3-[[2-(o-methoxyphenoxy)ethyl]amino]-2-propanol. Carvedilol is a racemic mixture with the following structure:

COREG is a white, oval, film-coated tablet containing 3.125 mg, 6.25 mg, 12.5 mg, or 25 mg of carvedilol. The 6.25-mg, 12.5-mg, and 25-mg tablets are TILTAB tablets. Inactive ingredients consist of colloidal silicon dioxide, crospovidone, hypromellose, lactose, magnesium stearate, polyethylene glycol, polysorbate 80, povidone, sucrose, and titanium dioxide.

Carvedilol is a white to off-white powder with a molecular weight of 406.5 and a molecular formula of C24H26N2O4. It is freely soluble in dimethylsulfoxide; soluble in methylene chloride and methanol; sparingly soluble in 95% ethanol and isopropanol; slightly soluble in ethyl ether; and practically insoluble in water, gastric fluid (simulated, TS, pH 1.1), and intestinal fluid (simulated, TS without pancreatin, pH 7.5).

12 CLINICAL PHARMACOLOGY

12.1 Mechanism of Action

COREG is a racemic mixture in which nonselective β-adrenoreceptor blocking activity is present in the S(-) enantiomer and α1-adrenergic blocking activity is present in both R(+) and S(-) enantiomers at equal potency. COREG has no intrinsic sympathomimetic activity.

12.2 Pharmacodynamics

Heart Failure

The basis for the beneficial effects of COREG in heart failure is not established.

Two placebo‑controlled trials compared the acute hemodynamic effects of COREG with baseline measurements in 59 and 49 subjects with NYHA class II‑IV heart failure receiving diuretics, ACE inhibitors, and digitalis. There were significant reductions in systemic blood pressure, pulmonary artery pressure, pulmonary capillary wedge pressure, and heart rate. Initial effects on cardiac output, stroke volume index, and systemic vascular resistance were small and variable.

These trials measured hemodynamic effects again at 12 to 14 weeks. COREG significantly reduced systemic blood pressure, pulmonary artery pressure, right atrial pressure, systemic vascular resistance, and heart rate, while stroke volume index was increased.

Among 839 subjects with NYHA class II‑III heart failure treated for 26 to 52 weeks in 4 U.S. placebo‑controlled trials, average left ventricular ejection fraction (EF) measured by radionuclide ventriculography increased by 9 EF units (%) in subjects receiving COREG and by 2 EF units in placebo subjects at a target dose of 25 to 50 mg twice daily. The effects of carvedilol on ejection fraction were related to dose. Doses of 6.25 mg twice daily, 12.5 mg twice daily, and 25 mg twice daily were associated with placebo‑corrected increases in EF of 5 EF units, 6 EF units, and 8 EF units, respectively; each of these effects were nominally statistically significant.

Left Ventricular Dysfunction following Myocardial Infarction

The basis for the beneficial effects of COREG in patients with left ventricular dysfunction following an acute myocardial infarction is not established.

Hypertension

The mechanism by which β-blockade produces an antihypertensive effect has not been established.

β-adrenoreceptor blocking activity has been demonstrated in animal and human studies showing that carvedilol (1) reduces cardiac output in normal subjects, (2) reduces exercise- and/or isoproterenol-induced tachycardia, and (3) reduces reflex orthostatic tachycardia. Significant β-adrenoreceptor blocking effect is usually seen within 1 hour of drug administration.

α1-adrenoreceptor blocking activity has been demonstrated in human and animal studies, showing that carvedilol (1) attenuates the pressor effects of phenylephrine, (2) causes vasodilation, and (3) reduces peripheral vascular resistance. These effects contribute to the reduction of blood pressure and usually are seen within 30 minutes of drug administration.

Due to the α1-receptor blocking activity of carvedilol, blood pressure is lowered more in the standing than in the supine position, and symptoms of postural hypotension (1.8%), including rare instances of syncope, can occur. Following oral administration, when postural hypotension has occurred, it has been transient and is uncommon when COREG is administered with food at the recommended starting dose and titration increments are closely followed [see Dosage and Administration (2)].

In hypertensive patients with normal renal function, therapeutic doses of COREG decreased renal vascular resistance with no change in glomerular filtration rate or renal plasma flow. Changes in excretion of sodium, potassium, uric acid, and phosphorus in hypertensive patients with normal renal function were similar after COREG and placebo.

COREG has little effect on plasma catecholamines, plasma aldosterone, or electrolyte levels, but it does significantly reduce plasma renin activity when given for at least 4 weeks. It also increases levels of atrial natriuretic peptide.

12.3 Pharmacokinetics

COREG is rapidly and extensively absorbed following oral administration, with absolute bioavailability of approximately 25% to 35% due to a significant degree of first-pass metabolism. Following oral administration, the apparent mean terminal elimination half-life of carvedilol generally ranges from 7 to 10 hours. Plasma concentrations achieved are proportional to the oral dose administered. When administered with food, the rate of absorption is slowed, as evidenced by a delay in the time to reach peak plasma levels, with no significant difference in extent of bioavailability. Taking COREG with food should minimize the risk of orthostatic hypotension.

Carvedilol is extensively metabolized. Following oral administration of radiolabeled carvedilol to healthy volunteers, carvedilol accounted for only about 7% of the total radioactivity in plasma as measured by area under the curve (AUC). Less than 2% of the dose was excreted unchanged in the urine. Carvedilol is metabolized primarily by aromatic ring oxidation and glucuronidation. The oxidative metabolites are further metabolized by conjugation via glucuronidation and sulfation. The metabolites of carvedilol are excreted primarily via the bile into the feces. Demethylation and hydroxylation at the phenol ring produce 3 active metabolites with β-receptor blocking activity. Based on preclinical studies, the 4'-hydroxyphenyl metabolite is approximately 13 times more potent than carvedilol for β-blockade.

Compared with carvedilol, the 3 active metabolites exhibit weak vasodilating activity. Plasma concentrations of the active metabolites are about one-tenth of those observed for carvedilol and have pharmacokinetics similar to the parent.

Carvedilol undergoes stereoselective first-pass metabolism with plasma levels of R(+)- carvedilol approximately 2 to 3 times higher than S(-)-carvedilol following oral administration in healthy subjects. The mean apparent terminal elimination half-lives for R(+)-carvedilol range from 5 to 9 hours compared with 7 to 11 hours for the S(-)- enantiomer.

The primary P450 enzymes responsible for the metabolism of both R(+) and S(-)- carvedilol in human liver microsomes were CYP2D6 and CYP2C9 and to a lesser extent YP3A4, 2C19, 1A2, and 2E1. CYP2D6 is thought to be the major enzyme in the 4'- and 5'-hydroxylation of carvedilol, with a potential contribution from 3A4. CYP2C9 is thought to be of primary importance in the O-methylation pathway of S(-)-carvedilol.

Carvedilol is subject to the effects of genetic polymorphism with poor metabolizers of debrisoquin (a marker for cytochrome P450 2D6) exhibiting 2- to 3-fold higher plasma concentrations of R(+)-carvedilol compared with extensive metabolizers. In contrast, plasma levels of S(-)-carvedilol are increased only about 20% to 25% in poor metabolizers, indicating this enantiomer is metabolized to a lesser extent by cytochrome P450 2D6 than R(+)-carvedilol. The pharmacokinetics of carvedilol do not appear to be different in poor metabolizers of S-mephenytoin (patients deficient in cytochrome P450 2C19).

Carvedilol is more than 98% bound to plasma proteins, primarily with albumin. The plasma-protein binding is independent of concentration over the therapeutic range. Carvedilol is a basic, lipophilic compound with a steady-state volume of distribution of approximately 115 L, indicating substantial distribution into extravascular tissues. Plasma clearance ranges from 500 to 700 mL/min.

12.4 Specific Populations

Heart Failure

Steady‑state plasma concentrations of carvedilol and its enantiomers increased proportionally over the 6.25- to 50- mg dose range in subjects with heart failure. Compared with healthy subjects, subjects with heart failure had increased mean AUC and Cmax values for carvedilol and its enantiomers, with up to 50% to 100% higher values observed in 6 subjects with NYHA class IV heart failure. The mean apparent terminal elimination half‑life for carvedilol was similar to that observed in healthy subjects.

Geriatric

Plasma levels of carvedilol average about 50% higher in the elderly compared with young subjects.

Hepatic Impairment

Compared with healthy subjects, patients with severe liver impairment (cirrhosis) exhibit a 4- to 7-fold increase in carvedilol levels. Carvedilol is contraindicated in patients with severe liver impairment.

Renal Impairment

Although carvedilol is metabolized primarily by the liver, plasma concentrations of carvedilol have been reported to be increased in patients with renal impairment. Based on mean AUC data, approximately 40% to 50% higher plasma concentrations of carvedilol were observed in subjects with hypertension and moderate to severe renal impairment compared with a control group of subjects with hypertension and normal renal function. However, the ranges of AUC values were similar for both groups. Changes in mean peak plasma levels were less pronounced, approximately 12% to 26% higher in subjects with impaired renal function.

Consistent with its high degree of plasma protein‑binding, carvedilol does not appear to be cleared significantly by hemodialysis.

12.5 Drug-Drug Interactions

Since carvedilol undergoes substantial oxidative metabolism, the metabolism and pharmacokinetics of carvedilol may be affected by induction or inhibition of cytochrome P450 enzymes.

Amiodarone

In a pharmacokinetic trial conducted in 106 Japanese subjects with heart failure, coadministration of small loading and maintenance doses of amiodarone with carvedilol resulted in at least a 2-fold increase in the steady-state trough concentrations of S(-)- carvedilol [see Drug Interactions (7.6)].

Cimetidine

In a pharmacokinetic trial conducted in 10 healthy male subjects, cimetidine (1,000 mg per day) increased the steady-state AUC of carvedilol by 30% with no change in Cmax [see Drug Interactions (7.5)].

Digoxin

Following concomitant administration of carvedilol (25 mg once daily) and digoxin (0.25 mg once daily) for 14 days, steady-state AUC and trough concentrations of digoxin were increased by 14% and 16%, respectively, in 12 subjects with hypertension [see Drug Interactions (7.4)].

Glyburide

In 12 healthy subjects, combined administration of carvedilol (25 mg once daily) and a single dose of glyburide did not result in a clinically relevant pharmacokinetic interaction for either compound.

Hydrochlorothiazide

A single oral dose of carvedilol 25 mg did not alter the pharmacokinetics of a single oral dose of hydrochlorothiazide 25 mg in 12 subjects with hypertension. Likewise, hydrochlorothiazide had no effect on the pharmacokinetics of carvedilol.

Rifampin

In a pharmacokinetic trial conducted in 8 healthy male subjects, rifampin (600 mg daily for 12 days) decreased the AUC and Cmax of carvedilol by about 70% [see Drug Interactions (7.5)].

Torsemide

In a trial of 12 healthy subjects, combined oral administration of carvedilol 25 mg once daily and torsemide 5 mg once daily for 5 days did not result in any significant differences in their pharmacokinetics compared with administration of the drugs alone.

Warfarin

Carvedilol (12.5 mg twice daily) did not have an effect on the steady-state prothrombin time ratios and did not alter the pharmacokinetics of R(+)- and S(-)-warfarin following concomitant administration with warfarin in 9 healthy volunteers.

13 NONCLINICAL TOXICOLOGY

13.1 Carcinogenesis, Mutagenesis, Impairment of Fertility

In 2-year studies conducted in rats given carvedilol at doses up to 75 mg per kg per day (12 times the MRHD as mg per m2) or in mice given up to 200 mg per kg per day (16 times the MRHD as mg per m2), carvedilol had no carcinogenic effect.

Carvedilol was negative when tested in a battery of genotoxicity assays, including the Ames and the CHO/HGPRT assays for mutagenicity and the in vitro hamster micronucleus and in vivo human lymphocyte cell tests for clastogenicity.

In a combined fertility/developmental/post-natal toxicity study, rats were given carvedilol (12, 60, 300 mg per kg per day) orally by gavage for 2 weeks before mating and through mating, gestation, and weaning for females and for 62 days prior to and through mating for males. At a dosage of 300 mg per kg per day (greater than or equal to 50 times the MRHD as mg per m2) carvedilol was toxic to adult rats (sedation, reduced weight gain) and was associated with a reduced number of successful matings, prolonged mating time, fewer corpora lutea and implants per dam, fewer live pups per litter, and delays in physical growth/development. The no-effect level for overt toxicity and impairment of fertility was 60 mg per kg per day (10 times the MRHD as mg per m2).

14 CLINICAL STUDIES

14.1 Heart Failure

A total of 6,975 subjects with mild-to-severe heart failure were evaluated in placebo- controlled trials of carvedilol.

Mild-to-Moderate Heart Failure

Carvedilol was studied in 5 multicenter, placebo‑controlled trials, and in 1 active- controlled trial (COMET trial) involving subjects with mild-to-moderate heart failure.

Four U.S. multicenter, double‑blind, placebo‑controlled trials enrolled 1,094 subjects (696 randomized to carvedilol) with NYHA class II‑III heart failure and ejection fraction less than or equal to 0.35. The vast majority were on digitalis, diuretics, and an ACE inhibitor at trial entry. Patients were assigned to the trials based upon exercise ability. An Australia‑New Zealand double‑blind, placebo‑controlled trial enrolled 415 subjects (half randomized to carvedilol) with less severe heart failure. All protocols excluded subjects expected to undergo cardiac transplantation during the 7.5 to 15 months of double‑blind follow‑up. All randomized subjects had tolerated a 2‑week course on carvedilol 6.25 mg twice daily.

In each trial, there was a primary end point, either progression of heart failure (1 U.S. trial) or exercise tolerance (2 U.S. trials meeting enrollment goals and the Australia‑New Zealand trial). There were many secondary end points specified in these trials, including NYHA classification, patient and physician global assessments, and cardiovascular hospitalization. Other analyses not prospectively planned included the sum of deaths and total cardiovascular hospitalizations. In situations where the primary end points of a trial do not show a significant benefit of treatment, assignment of significance values to the other results is complex, and such values need to be interpreted cautiously.

The results of the U.S. and Australia‑New Zealand trials were as follows:

Slowing Progression of Heart Failure: One U.S. multicenter trial (366 subjects) had as its primary end point the sum of cardiovascular mortality, cardiovascular hospitalization, and sustained increase in heart failure medications. Heart failure progression was reduced, during an average follow‑up of 7 months, by 48% (P = 0.008).

In the Australia‑New Zealand trial, death and total hospitalizations were reduced by about 25% over 18 to 24 months. In the 3 largest U.S. trials, death and total hospitalizations were reduced by 19%, 39%, and 49%, nominally statistically significant in the last 2 trials. The Australia‑New Zealand results were statistically borderline.

Functional Measures: None of the multicenter trials had NYHA classification as a primary end point, but all such trials had it as a secondary end point. There was at least a trend toward improvement in NYHA class in a l trials. Exercise tolerance was the primary end point in 3 trials; in none was a statistically significant effect found.

Subjective Measures: Health-related quality of life, as measured with a standard questionnaire (a primary end point in 1 trial), was unaffected by carvedilol. However, patients' and investigators' global assessments showed significant improvement in most trials.

Mortality: Death was not a pre-specified end point in any trial but was analyzed in all trials. Overall, in these 4 U.S. trials, mortality was reduced, nominally significantly so in 2 trials.

The COMET Trial

In this double-blind trial, 3,029 subjects with NYHA class II-IV heart failure (left ventricular ejection fraction less than or equal to 35%) were randomized to receive either carvedilol (target dose: 25 mg twice daily) or immediate-release metoprolol tartrate (target dose: 50 mg twice daily). The mean age of the subjects was approximately 62 years, 80% were males, and the mean left ventricular ejection fraction at baseline was 26%. Approximately 96% of the subjects had NYHA class II or III heart failure.

Concomitant treatment included diuretics (99%), ACE inhibitors (91%), digitalis (59%), aldosterone antagonists (11%), and "statin" lipid-lowering agents (21%). The mean duration of follow-up was 4.8 years. The mean dose of carvedilol was 42 mg per day.

The trial had 2 primary end points: all-cause mortality and the composite of death plus hospitalization for any reason. The results of COMET are presented in Table 3 below. All- cause mortality carried most of the statistical weight and was the primary determinant of the trial size. All-cause mortality was 34% in the subjects treated with carvedilol and was 40% in the immediate-release metoprolol group (P = 0.0017; hazard ratio = 0.83, 95% CI: 0.74 to 0.93). The effect on mortality was primarily due to a reduction in cardiovascular death. The difference between the 2 groups with respect to the composite end point was not significant (P = 0.122). The estimated mean survival was 8.0 years with carvedilol and 6.6 years with immediate-release metoprolol.

Table 3. Results of COMET
End Point | Carvedilol n = 1,511 | Metoprolol n = 1,518 | Hazard Ratio | (95% CI)
All-cause mortality | 34% | 40% | 0.83 | 0.74 – 0.93
Mortality + all hospitalization | 74% | 76% | 0.94 | 0.86 – 1.02
Cardiovascular death | 30% | 35% | 0.80 | 0.70 – 0.90
Sudden death | 14% | 17% | 0.81 | 0.68 – 0.97
Death due to circulatory failure | 11% | 13% | 0.83 | 0.67 – 1.02
Death due to stroke | 0.9% | 2.5% | 0.33 | 0.18 – 0.62

It is not known whether this formulation of metoprolol at any dose or this low dose of metoprolol in any formulation has any effect on survival or hospitalization in patients with heart failure. Thus, this trial extends the time over which carvedilol manifests benefits on survival in heart failure, but it is not evidence that carvedilol improves outcome over the formulation of metoprolol (TOPROL-XL) with benefits in heart failure.

Severe Heart Failure (COPERNICUS)

In a double-blind trial (COPERNICUS), 2,289 subjects with heart failure at rest or with minimal exertion and left ventricular ejection fraction less than 25% (mean 20%), despite digitalis (66%), diuretics (99%), and ACE inhibitors (89%), were randomized to placebo or carvedilol. Carvedilol was titrated from a starting dose of 3.125 mg twice daily to the maximum tolerated dose or up to 25 mg twice daily over a minimum of 6 weeks. Most subjects achieved the target dose of 25 mg. The trial was conducted in Eastern and Western Europe, the United States, Israel, and Canada. Similar numbers of subjects per group (about 100) withdrew during the titration period.

The primary end point of the trial was all ‑cause mortality, but cause‑specific mortality and the risk of death or hospitalization (total, cardiovascular [CV], or heart failure [HF]) were also examined. The developing trial data were followed by a data monitoring committee, and mortality analyses were adjusted for these multiple looks. The trial was stopped after a median follow‑up of 10 months because of an observed 35% reduction in mortality (from 19.7% per patient-year on placebo to 12.8% on carvedilol; hazard ratio 0.65, 95% CI: 0.52 to 0.81, P = 0.0014, adjusted) (see Figure 1). The results of COPERNICUS are shown in Table 4.

Table 4. Results of COPERNICUS Trial in Subjects with Severe Heart Failure
End Point | Placebo (n = 1,133) | Carvedilol (n = 1,156) | Hazard Ratio (95% CI) | % Reduction | Nominal P value
Mortality | 190 | 130 | 0.65 (0.52 – 0.81) | 35 | 0.00013
Mortality + all hospitalization | 507 | 425 | 0.76 (0.67 – 0.87) | 24 | 0.00004
Mortality + CV hospitalization | 395 | 314 | 0.73 (0.63 – 0.84) | 27 | 0.00002
Mortality + HF hospitalization | 357 | 271 | 0.69 (0.59 – 0.81) | 31 | 0.000004
Cardiovascular = CV; Heart failure = HF.

Figure 1. Survival Analysis for COPERNICUS (Intent-to-Treat)

The effect on mortality was principally the result of a reduction in the rate of sudden death among subjects without worsening heart failure.

Patients' global assessments, in which carvedilol‑treated subjects were compared with placebo, were based on pre-specified, periodic patient self-assessments regarding whether clinical status post-treatment showed improvement, worsening, or no change compared with baseline. Subjects treated with carvedilol showed significant improvements in global assessments compared with those treated with placebo in COPERNICUS.

The protocol also specified that hospitalizations would be assessed. Fewer subjects on COREG than on placebo were hospitalized for any reason (372 versus 432, P = 0.0029), for cardiovascular reasons (246 versus 314, P = 0.0003), or for worsening heart failure (198 versus 268, P = 0.0001).

COREG had a consistent and beneficial effect on all-cause mortality as well as the combined end points of all‑cause mortality plus hospitalization (total, CV, or for heart failure) in the overall trial population and in all subgroups examined, including men and women, elderly and non‑elderly, blacks and non‑blacks, and diabetics and non-diabetics (see Figure 2).

Figure 2. Effects on Mortality for Subgroups in COPERNICUS

14.2 Left Ventricular Dysfunction following Myocardial Infarction

CAPRICORN was a double‑blind trial comparing carvedilol and placebo in 1,959 subjects with a recent myocardial infarction (within 21 days) and left ventricular ejection fraction of less than or equal to 40%, with (47%) or without symptoms of heart failure. Subjects given carvedilol received 6.25 mg twice daily, titrated as tolerated to 25 mg twice daily. Subjects had to have a systolic blood pressure greater than 90 mm Hg, a sitting heart rate greater than 60 beats per minute, and no contraindication to β‑blocker use.

Treatment of the index infarction included aspirin (85%), IV or oral β‑blockers (37%), nitrates (73%), heparin (64%), thrombolytics (40%), and acute angioplasty (12%).

Background treatment included ACE inhibitors or angiotensin-receptor blockers (97%), anticoagulants (20%), lipid‑lowering agents (23%), and diuretics (34%). Baseline population characteristics included an average age of 63 years, 74% male, 95% Caucasian, mean blood pressure 121/74 mm Hg, 22% with diabetes, and 54% with a history of hypertension. Mean dosage achieved of carvedilol was 20 mg twice daily; mean duration of follow‑up was 15 months.

All‑cause mortality was 15% in the placebo group and 12% in the carvedilol group, indicating a 23% risk reduction in subjects treated with carvedilol (95% CI: 2% to 40%, P = 0.03), as shown in Figure 3. The effects on mortality in various subgroups are shown in Figure 4. Nearly all deaths were cardiovascular (which were reduced by 25% by carvedilol), and most of these deaths were sudden or related to pump failure (both types of death were reduced by carvedilol). Another trial end point, total mortality and all-cause hospitalization, did not show a significant improvement.

There was also a significant 40% reduction in fatal or non-fatal myocardial infarction observed in the group treated with carvedilol (95% CI: 11% to 60%, P = 0.01). A similar reduction in the risk of myocardial infarction was also observed in a meta-analysis of placebo- controlled trials of carvedilol in heart failure.

Figure 3. Survival Analysis for CAPRICORN (Intent-to-Treat)

Figure 4. Effects on Mortality for Subgroups in CAPRICORN

14.3 Hypertension

COREG was studied in 2 placebo‑controlled trials that utilized twice‑daily dosing at total daily doses of 12.5 to 50 mg. In these and other trials, the starting dose did not exceed 12.5 mg. At 50 mg per day, COREG reduced sitting trough (12‑hour) blood pressure by about 9/5.5 mm Hg; at 25 mg per day the effect was about 7.5/3.5 mm Hg. Comparisons of trough-to-peak blood pressure showed a trough-to-peak ratio for blood pressure response of about 65%. Heart rate fell by about 7.5 beats per minute at 50 mg per day. In general, as is true for other β‑blockers, responses were smaller in black than non‑black subjects. There were no age‑ or gender‑related differences in response.

The peak antihypertensive effect occurred 1 to 2 hours after a dose. The dose‑related blood pressure response was accompanied by a dose‑related increase in adverse effects [see Adverse Reactions (6)].

14.4 Hypertension with Type 2 Diabetes Mellitus

In a double-blind trial (GEMINI), COREG, added to an ACE inhibitor or angiotensin- receptor blocker, was evaluated in a population with mild‑to‑moderate hypertension and well-controlled type 2 diabetes mellitus. The mean HbA1c at baseline was 7.2%. COREG was titrated to a mean dose of 17.5 mg twice daily and maintained for 5 months. COREG had no adverse effect on glycemic control, based on HbA1c measurements (mean change from baseline of 0.02%, 95% CI: ‑0.06 to 0.10, P = NS) [see Warnings and Precautions (5.6)].

16 HOW SUPPLIED/STORAGE AND HANDLING

The white, oval, film‑coated tablets are available in the following strengths:

- 3.125 mg – engraved with "39" and "WP"
- 6.25 mg – engraved with "4140" and "WP"
- 12.5 mg – engraved with "4141" and "WP"
- 25 mg – engraved with "4142" and "WP"

The 6.25-mg, 12.5-mg, and 25-mg tablets are TILTAB tablets.

- 3.125 mg bottles of 100: NDC 80725-139-20
- 6.25 mg bottles of 100: NDC 80725-140-20
- 12.5 mg bottles of 100: NDC 80725-141-20
- 25 mg bottles of 100: NDC 80725 142-20

STORAGE AND HANDLING

Store below 30°C (86°F). Protect from moisture. Dispense in a tight, light‑resistant container.

17 PATIENT COUNSELING INFORMATION

Advise the patient to read the FDA-approved patient labeling (Patient Information).

Patients taking COREG should be advised of the following:

- Patients should take COREG with food.
- Patients should not interrupt or discontinue using COREG without a physician's advice.
- Patients with heart failure should consult their physician if they experience signs or symptoms of worsening heart failure such as weight gain or increasing shortness of breath.
- Patients may experience a drop in blood pressure when standing, resulting in dizziness and, rarely, fainting. Patients should sit or lie down when these symptoms of lowered blood pressure occur.
- If experiencing dizziness or fatigue, patients should avoid driving or hazardous tasks.
- Patients should consult a physician if they experience dizziness or faintness, in case the dosage should be adjusted.
- Inform patients or caregivers that there is a risk of hypoglycemia when COREG is given to patients who are fasting or who are vomiting. Instruct patients or caregivers how to monitor for signs of hypoglycemia [see Warnings and Precautions (5.6)].
- Contact lens wearers may experience decreased lacrimation.

COREG, COREG CR, and TILTAB are trademarks used under license by Waylis Therapeutics LLC

The other brand listed is a trademark owned by or licensed to its owner and is not owned by or licensed to Waylis Therapeutics LLC. The maker of this brand is not affiliated with and does not endorse Waylis Therapeutics LLC or its products.

Manufactured for

Waylis Therapeutics LLC

Wixom, MI 48393

October 2023

PATIENT INFORMATION COREG (Co-REG) (carvedilol) tablets

Read the Patient Information that comes with COREG before you start taking it and each time you get a refill. There may be new information. This information does not take the place of talking with your doctor about your medical condition or your treatment. If you have any questions about COREG, ask your doctor or pharmacist.

What is COREG?

COREG is a prescription medicine that belongs to a group of medicines called "beta- blockers". COREG is used, often with other medicines, for the following conditions:

- to treat patients with certain types of heart failure
- to treat patients who had a heart attack that worsened how well the heart pumps
- to treat patients with high blood pressure (hypertension)

COREG is not approved for use in children under 18 years of age.

Who should not take COREG?

Do not take COREG if you:

- have severe heart failure and are hospitalized in the intensive care unit or require certain intravenous medications that help support circulation (inotropic medications).
- are prone to asthma or other breathing problems.
- have a slow heartbeat or a heart that skips a beat (irregular heartbeat).
- have liver problems.
- are allergic to any of the ingredients in COREG. The active ingredient is carvedilol. See the end of this leaflet for a list of all the ingredients in COREG.

What should I tell my doctor before taking COREG?

Tell your doctor about all of your medical conditions, including if you:

- have asthma or other lung problems (such as bronchitis or emphysema).
- have problems with blood flow in your feet and legs (peripheral vascular disease). COREG can make some of your symptoms worse.
- have diabetes.
- have thyroid problems.
- have a condition called pheochromocytoma.
- have had severe allergic reactions.
- are pregnant or trying to become pregnant. It is not known if COREG is safe for your unborn baby. You and your doctor should talk about the best way to control your high blood pressure during pregnancy.
- are breastfeeding. It is not known if COREG passes into your breast milk. Talk with your doctor about the best way to feed your baby if you are taking COREG.
- are scheduled for surgery and will be given anesthetic agents.
- are scheduled for cataract surgery and have taken or are currently taking COREG.
- are taking prescription or over-the-counter medicines, vitamins, and herbal supplements. COREG and certain other medicines can affect each other and cause serious side effects. COREG may affect the way other medicines work. Also, other medicines may affect how well COREG works.

Keep a list of all the medicines you take. Show this list to your doctor and pharmacist before you start a new medicine.

How should I take COREG?

It is important for you to take your medicine every day as directed by your doctor. If you stop taking COREG suddenly, you could have chest pain and/or a heart attack. If your doctor decides that you should stop taking COREG, your doctor may slowly lower your dose over a period of time before stopping it completely.

- Take COREG exactly as prescribed. Your doctor will tell you how many tablets to take and how often. In order to minimize possible side effects, your doctor might begin with a low dose and then slowly increase the dose.
  - Do not stop taking COREG and do not change the amount of COREG you take without talking to your doctor.
- Tell your doctor if you gain weight or have trouble breathing while taking COREG.
- Take COREG with food.
- If you miss a dose of COREG, take your dose as soon as you remember, unless it is time to take your next dose. Take your next dose at the usual time. Do not take 2 doses at the same time.
- If you take too much COREG, call your doctor or poison control center right away.

What should I avoid while taking COREG?

- COREG can cause you to feel dizzy, tired, or faint. Do not drive a car, use machinery, or do anything that needs you to be alert if you have these symptoms.

What are possible side effects of COREG?

- Low blood pressure (which may cause dizziness or fainting when you stand up).
  If these happen, sit or lie down right away and tell your doctor.
- Tiredness. If you feel tired or dizzy you should not drive, use machinery, or do anything that needs you to be alert.
- Slow heartbeat.
- Changes in your blood sugar. If you have diabetes, tell your doctor if you have any changes in your blood sugar levels.
- COREG may hide some of the symptoms of low blood sugar, especially a fast heartbeat.
- COREG may mask the symptoms of hyperthyroidism (overactive thyroid).
- Worsening of severe allergic reactions.
- Rare but serious allergic reactions (including hives or swelling of the face, lips, tongue, and/or throat that may cause difficulty in breathing or swallowing) have happened in patients who were on COREG. These reactions can be life-threatening.

Other side effects of COREG include shortness of breath, weight gain, diarrhea, and fewer tears or dry eyes that become bothersome if you wear contact lenses.

Call your doctor if you have any side effects that bother you or don't go away.

Call your doctor for medical advice about side effects. You may report side effects to FDA at 1-800-FDA-1088.

How should I store COREG?

- Store COREG at less than 86°F (30°C). Keep the tablets dry.
- Safely, throw away COREG that is out of date or no longer needed.
- Keep COREG and all medicines out of the reach of children.

General Information about COREG

Medicines are sometimes prescribed for conditions other than those described in patient information leaflets. Do not use COREG for a condition for which it was not prescribed. Do not give COREG to other people, even if they have the same symptoms you have. It may harm them.

This leaflet summarizes the most important information about COREG. If you would like more information, talk with your doctor. You can ask your doctor or pharmacist for information about COREG that is written for healthcare professionals.

What are the ingredients in COREG?

Active Ingredient: carvedilol.

Inactive Ingredients: colloidal silicon dioxide, crospovidone, hypromellose, lactose, magnesium stearate, polyethylene glycol, polysorbate 80, povidone, sucrose, and titanium dioxide.

Carvedilol tablets come in the following strengths: 3.125 mg, 6.25 mg, 12.5 mg, 25 mg.

What is high blood pressure (hypertension)?

Blood pressure is the force of blood in your blood vessels when your heart beats and when your heart rests. You have high blood pressure when the force is too much. High blood pressure makes the heart work harder to pump blood through the body and causes damage to blood vessels. COREG can help your blood vessels relax so your blood pressure is lower. Medicines that lower blood pressure may lower your chance of having a stroke or heart attack.

COREG is a trademark used under license by Waylis Therapeutics LLC.

Manufactured for

Waylis Therapeutics LLC

Wixom, MI 48393

October 2023

PRINCIPAL DISPLAY PANEL - 3.125 mg Tablet Bottle Label

NDC 80725-139-20

Waylis
THERAPEUTICS

COREG
(carvedilol) Tablets

3.125 mg

Rx only
100 Tablets

PRINCIPAL DISPLAY PANEL - 6.25 mg Tablet Bottle Label

NDC 80725-140-20

Waylis
THERAPEUTICS

COREG
(carvedilol) Tablets

6.25 mg

Rx only
100 TILTAB Tablets

PRINCIPAL DISPLAY PANEL - 12.5 mg Tablet Bottle Label

NDC 80725-141-20

Waylis
THERAPEUTICS

COREG
(carvedilol) Tablets

12.5 mg

Rx only
100 TILTAB Tablets

PRINCIPAL DISPLAY PANEL - 25 mg Tablet Bottle Label

NDC 80725-142-20

Waylis
THERAPEUTICS

COREG
(carvedilol) Tablets

25 mg

Rx only
100 TILTAB Tablets